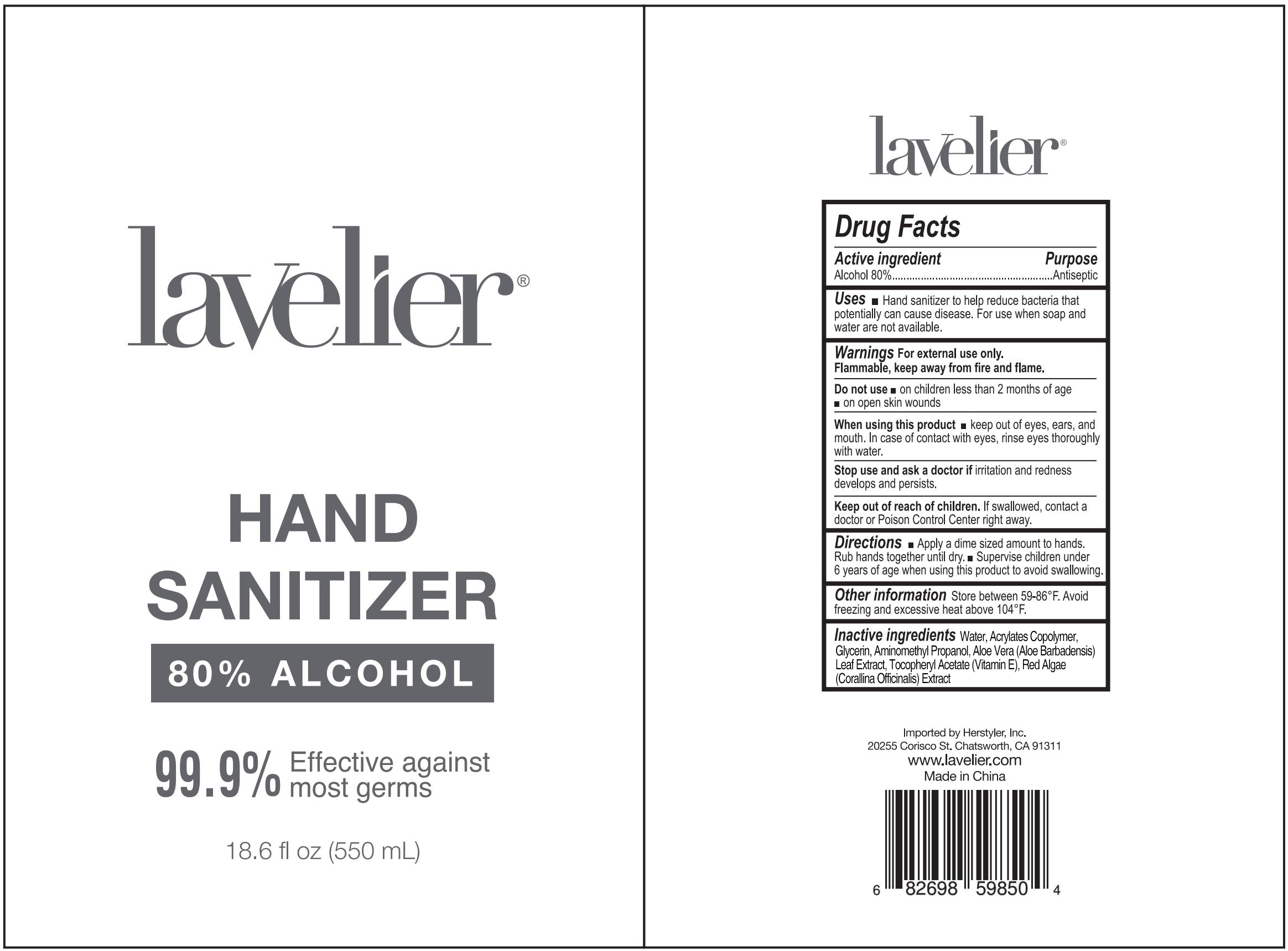 DRUG LABEL: Hand Sanitizer
NDC: 76383-022 | Form: LIQUID
Manufacturer: BBC GROUP LIMITED
Category: otc | Type: HUMAN OTC DRUG LABEL
Date: 20200523

ACTIVE INGREDIENTS: ALCOHOL 80 mL/100 mL
INACTIVE INGREDIENTS: CORALLINA OFFICINALIS; ALOE VERA LEAF; GLYCERIN; WATER; .ALPHA.-TOCOPHEROL ACETATE; AMINOMETHYLPROPANOL

lavelier Hand Sanitizer

Active Ingredient

Alcohol 80%

Purpose

Antiseptic

Uses

■ Hand sanitizer to help reduce bacteria that potentially can cause disease. For use when soap and water are not available

Warnings

For external use only. Flammable, keep away from fire and flame.

Do not use

■ on children less than 2 months of age ■ on open skin wounds

When using this product

■ keep out of eyes, ears, and mouth. In case of contact with eyes, rinse eyes throughly with water.

Stop use and ask a doctor if

irritation and redness develops and persists.

Keep out of reach of children

If swallowed, contact a doctor or Poison Control Center right away.

Directions

■ Apply a dime sized amount to hands. Rub hands together until dry ■ Supervise children under 6 years of age when using this product to avoid swallowing

Other information

Store between 59-86ºF. Avoid freezing and excessive heat above 104ºF

Inactive ingredients

Water, Acrylates Copolymer, Glycerin, Aminomethyl Propanol, Aloe Vera (Aloe Barbadensis) Leaf Extract, Tocopheryl Acetate (Vitamin E), Red Algae (Corallina Officinalis) Extract